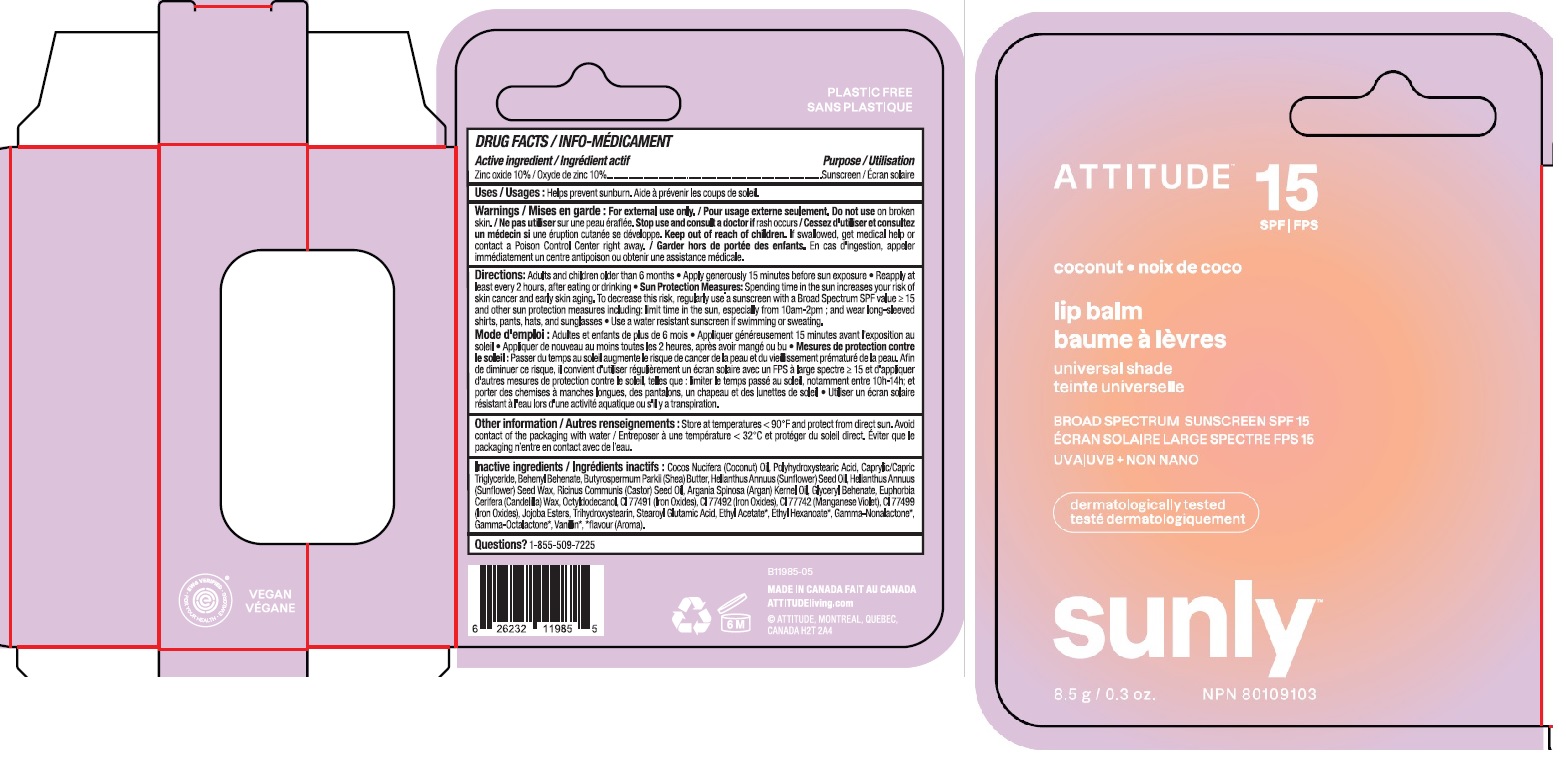 DRUG LABEL: Attitude - Lip Balm - SPF 15 - Coconut
NDC: 61649-985 | Form: STICK
Manufacturer: Attitude DBA 9055-7588 Québec Inc.
Category: otc | Type: HUMAN OTC DRUG LABEL
Date: 20251203

ACTIVE INGREDIENTS: ZINC OXIDE 10 g/100 g
INACTIVE INGREDIENTS: FERRIC OXIDE RED; FERRIC OXIDE YELLOW; FERROSOFERRIC OXIDE; TRIHYDROXYSTEARIN; BEHENYL BEHENATE; GLYCERYL MONOBEHENATE; OCTYLDODECANOL; COCONUT OIL; POLYHYDROXYSTEARIC ACID (2300 MW); SHEA BUTTER; SUNFLOWER OIL; HELIANTHUS ANNUUS SEED WAX; MEDIUM-CHAIN TRIGLYCERIDES; CASTOR OIL; ARGAN OIL; CANDELILLA WAX; VANILLIN; .GAMMA.-OCTALACTONE; .GAMMA.-NONALACTONE; ETHYL CAPROATE; ETHYL ACETATE; MANGANESE VIOLET; JOJOBA OIL, RANDOMIZED; STEAROYL GLUTAMIC ACID

ATTITUDE Sunly Lip Balm - Coconut - SPF 15

DRUG FACTS

Medicinal ingredient

Zinc oxide (10%)

Purpose

Sunscreen

Uses

Helps prevent sunburn.

Warnings

For external use only.

Do not use on broken skin.

Keep out of reach of children.If swallowed, get medical help or contact a Poison Control Center right away.

Stop use and consult a doctor if rash occurs.

Directions

Adults and children older than 6 months.

- Apply generously 15 minutes before sun exposure.
- Reapply at least every 2 hours, after eating or drinking.
- Sun Protection Measures: Spending time in the sun increases your risk of skin cancer and early aging. To decrease this risk, regularly use a sunscreen with a Broad Spectrum SPFvalue of 15 or higher and other sun protection measures including: limit time in the sun, especially from 10am-2pm; and wear long-sleeved shirts, pants, hats and sunglasses.
- Use a water resistant sunscreen if swimming or sweating.

Inactive or non-medicinal ingredients

Cocos Nucifera (Coconut) Oil, Polyhydroxystearic Acid, Caprylic/Capric Triglyceride, Behenyl Behenate, Butyrospermum Parkii (Shea) Butter, Helianthus Annuus (Sunflower) Seed Oil, Helianthus Annuus (Sunflower) Seed Wax, Ricinus Communis (Castor) Seed Oil, Argania Spinosa (Argan) Kernel Oil, Glyceryl Behenate, Euphorbia Cerifera (Candelilla) Wax, Octyldodecanol, CI 77491 (Iron Oxides), CI 77492 (Iron Oxides), CI 77742 (Manganese Violet), CI 77499 (Iron Oxides), Jojoba Esters, Trihydroxystearin, Stearoyl Glutamic Acid, Ethyl Acetate*, Ethyl Hexanoate*, Gamma-Nonalactone*, Gamma-Octalactone*, Vanillin*, *flavour (Aroma).

Other Information

Store at temperatures < 90F and protect from direct sun. Avoid contact of packaging with water.

Questions ? 1-855-509-7225

RECENT MAJOR CHANGES

Update of the directions

PRINCIPAL DISPLAY PANEL - 8.5 g Tube Carton

ATTITUDE

natural care

SPF 15

coconut

lip balm

universal shade

BROAD SPECTRUM SUNSCREEN SPF 15

UVA UVB + NON NANO

SUNLY

8.5 g / 0.3 oz.

NPN 80109103

Vegan

EWG Verified

Ocean Lovers

Dermatologically tested